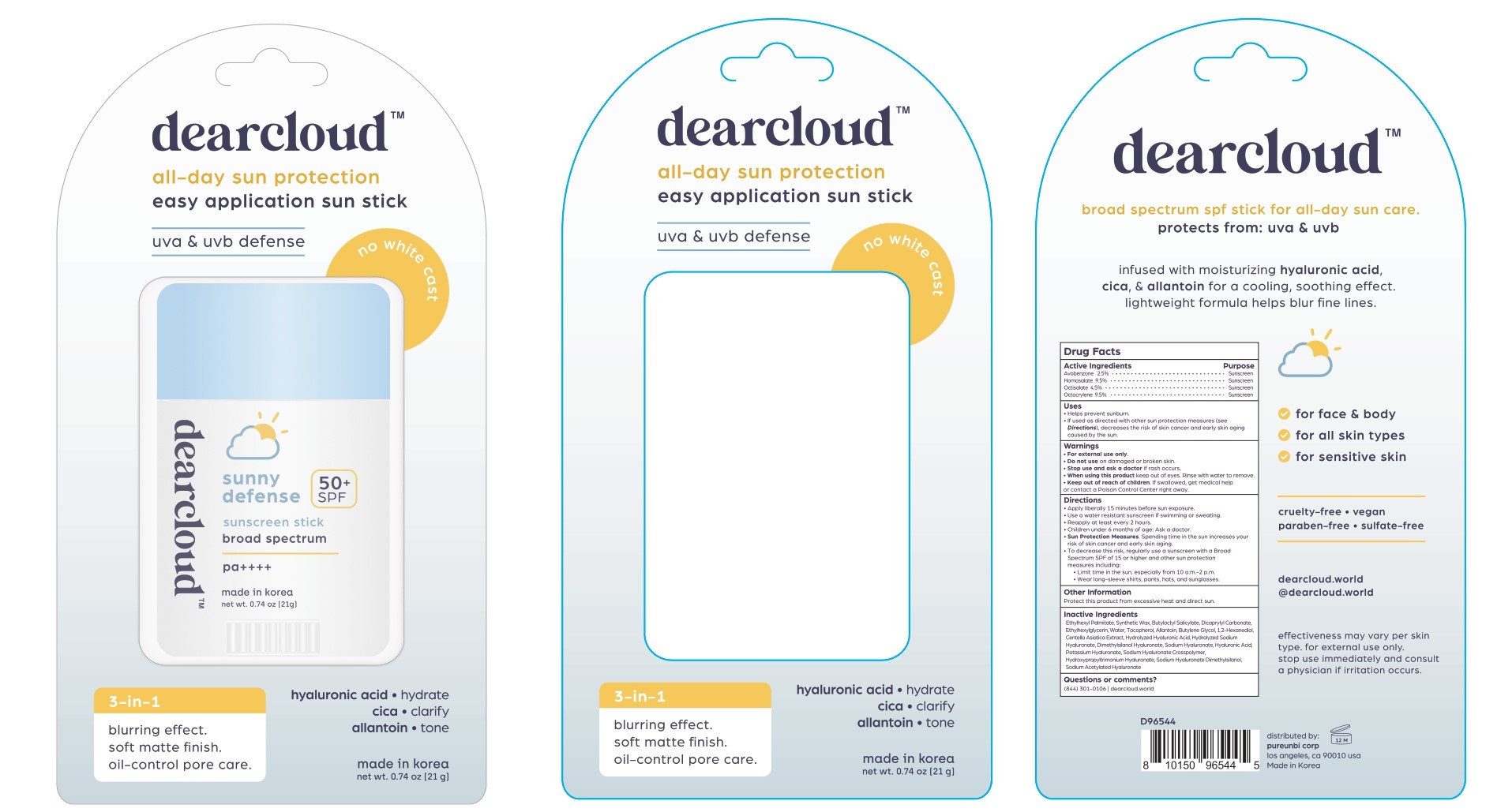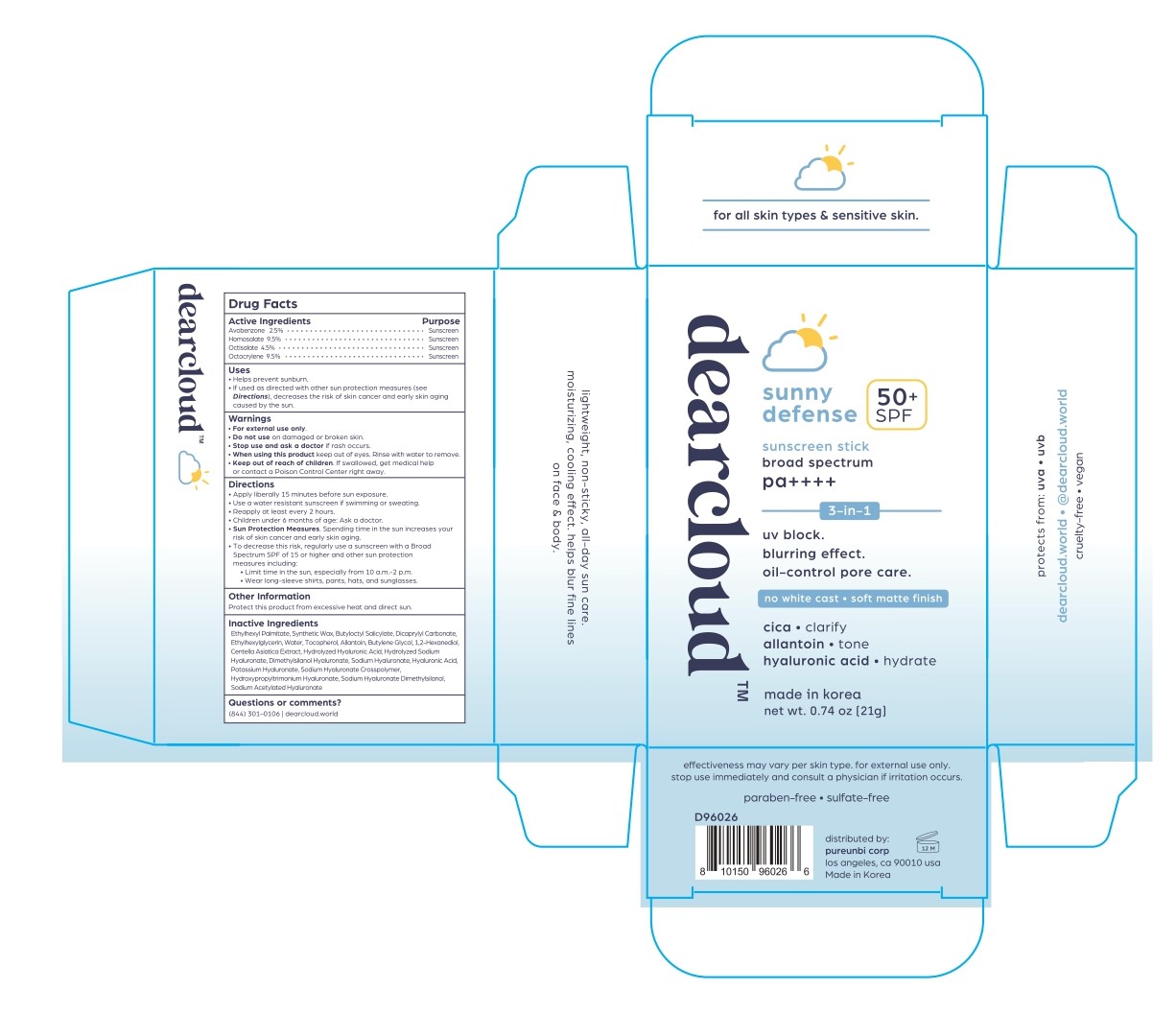 DRUG LABEL: Sunny Defense Sunscreen Stick
NDC: 84326-524 | Form: STICK
Manufacturer: RBGROUP Co., Ltd
Category: otc | Type: HUMAN OTC DRUG LABEL
Date: 20251117

ACTIVE INGREDIENTS: OCTOCRYLENE 1.995 g/21 g; AVOBENZONE 0.525 g/21 g; OCTISALATE 0.945 g/21 g; HOMOSALATE 1.995 g/21 g
INACTIVE INGREDIENTS: DIMETHYLSILANOL HYALURONATE; SODIUM ACETYLATED HYALURONATE; HYALURONATE SODIUM; HYALURONIC ACID; BUTYLOCTYL SALICYLATE; .ALPHA.-TOCOPHEROL, D-; BUTYLENE GLYCOL; ETHYLHEXYLGLYCERIN; WATER; CENTELLA ASIATICA TRITERPENOIDS; 1,2-HEXANEDIOL; ETHYLHEXYL PALMITATE; ALLANTOIN; SYNTHETIC WAX (1900 MW); DICAPRYLYL CARBONATE

84326-524 Sunny Defense Sunscreen Stick

ACTIVE INGREDIENT

Avobenzone 2.5%

Homosalate 9.5%

Octisalate 4.5%

Octocrylene 9.5%

PURPOSE

Sunscreen

INDICATIONS AND USAGE

● Helps prevent sunburn.

● If used as directed with other sun protection measures (see Directions), decreases the risk of skin cancer and early skin aging caused by the sun.

WARNINGS

For external use only

DO NOT USE

● on damaged or broken skin

WHEN USING

this product ● keep out of eyes. Rinse with water to remove.

STOP USE

and ask a doctor if rash occurs.

KEEP OUT OF REACH OF CHILDREN

If swallowed, get medical help or contact a Poison Control Center right away.

OTHER SAFETY INFORMATION

● Protect this product from excessive heat and direct sun.

Directions

● Apply liberally 15 minutes before sun exposure.

● Use a water resistant sunscreen if swimming or sweating.

● Reapply at least every 2 hours.

● Children under 6 months of age: Ask a doctor.

● Sun Protection Measures. Spending time in the sun increases your risk of skin cancer and early skin aging. ● To decrease this risk, regularly use a sunscreen with a Broad Spectrum SPF of 15 or higher and other sun protection measures including: ● Limit time in the sun, especially from 10 a.m.-2 p.m. ● Wear long-sleeve shirts, pants, hats, and sunglasses.

INACTIVE INGREDIENT

Ethylhexyl Palmitate, Synthetic Wax, Butyloctyl Salicylate, Dicaprylyl Carbonate, Ethylhexylglycerin, Water, Tocopherol, Allantoin, Butylene Glycol, 1,2-Hexanediol, Centella Asiatica Extract, Hydrolyzed Hyaluronic Acid, Hydrolyzed Sodium Hyaluronate, Dimethylsilanol Hyaluronate, Sodium Hyaluronate, Hyaluronic Acid, Potassium Hyaluronate, Sodium Hyaluronate Crosspolymer, Hydroxypropyltrimonium Hyaluronate, Sodium Hyaluronate Dimethylsilanol, Sodium Acetylated Hyaluronate